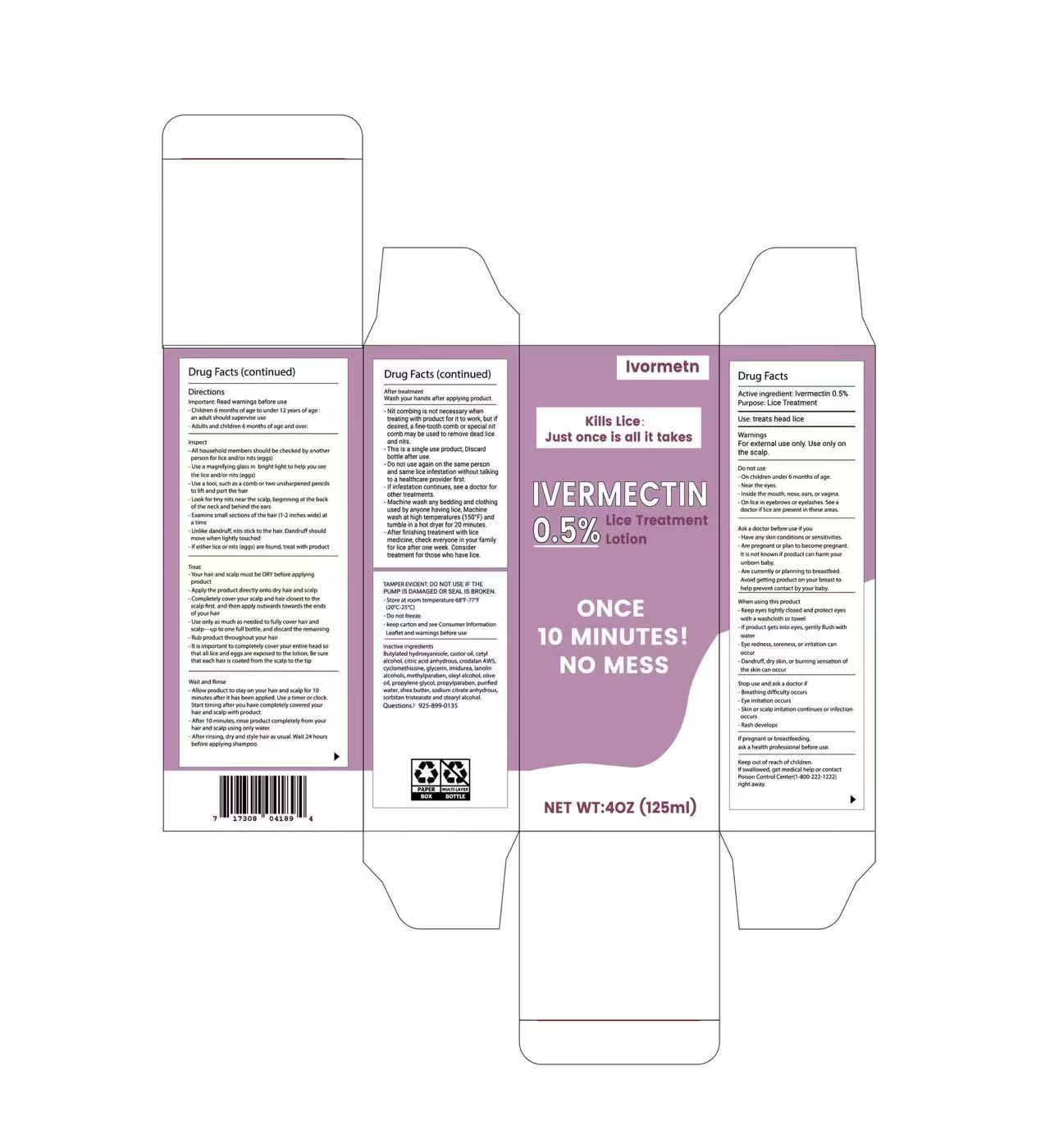 DRUG LABEL: lice treatment dedicated
NDC: 87276-001 | Form: LOTION
Manufacturer: Shenzhen Zhenshangzekai Technology Co., Ltd.
Category: otc | Type: HUMAN OTC DRUG LABEL
Date: 20251212

ACTIVE INGREDIENTS: IVERMECTIN 0.5 g/100 g
INACTIVE INGREDIENTS: CETYL ALCOHOL; STEARYL ALCOHOL; CASTOR OIL; CYCLOMETHICONE; BUTYLATED HYDROXYANISOLE; SORBITAN TRISTEARATE; SODIUM CITRATE; OLEYL ALCOHOL; PROPYLPARABEN; WATER; ANHYDROUS CITRIC ACID; LANOLIN ALCOHOLS; OLIVE OIL; GLYCERIN; PROPYLENE GLYCOL; METHYLPARABEN; IMIDUREA; SHEA BUTTER

ACTIVE INGREDIENT

Ivermectin 0.5%

ASK DOCTOR

Have any skin conditions or sensitivities.

Are pregnant or plan to become pregnant.
It is not known if product can harm your unborn baby.

Are currently or planning to breastfeed.
Avoid getting product on your breast to help prevent contact by your baby.

DO NOT USE

Breathing difficulty occurs.

Eye irritation occurs.

Skin or scalp irritation continues or infection occurs.

Rash develops.

Keep out of reach of children.
If swallowed, get medical help or contact Poison Control Center (1-800-222-1222) right away.

PREGNANCY OR BREAST FEEDING

If pregnant or breastfeeding, ask a health professional before use.

PURPOSE

Lice Treatment

QUESTIONS

925-899-0135

DOSAGE AND ADMINISTRATION

lotion, topical

WARNINGS

TAMPER EVIDENT: DO NOT USE IF THEPUMP IS DAMAGED OR SEAL IS BROKEN. Store at room temperature 68℃F-77°
Do not freeze.
keep carton and see Consumer Information Leaflet and warnings before use

INACTIVE INGREDIENT

Butylated hydroxyanisole, castor oil, cetyl alcohol, citric acid anhydrous, crodalan AWS,cyclomethicone, glycerin, imidurea, lanolinalcohols, methylparaben, oleyl alcohol, olive oil, propylene glycol, propylparaben, purified water, shea butter, sodium ditrate anhydrous,sorbitan tristearate and stearyl alcohol.

Directions
Important: Read warnings before use
.Children 6 months of age to under 12 years of age :
an adult should supervise use
Adults and children 6 months of age and over:
Inspect
All houschold members should be checked by anothe!person for lice and/or nits (eggs)
Use a magnifying glassin bright light to help you see
thelice and/or nits(eggs)
Use a tool, such as a comb or two unsharpened pencilsto lift and part the hair
Look for tiny nits near the scalp, beginning at the backof theneck and behind the ears
Examine small sections ofthe hair (1-2 inches wide) ata time
.Unlike dandruff, nits stick to the hair, Dandruff shouldmove when lightly touched
If either lice or nits (eggs) are found, treat with product
Treat
Your hair and scalp must be DRY before applyingproduct
Apply the product directly onto dry hair and scalp
Completely cover your scalp and hair closest to thescalp first.and then apply outwards towards the endsofyour hair
Use only as much asneeded to fully cover hair andscalp up to one full bottle, and discard the remainingRub product throughout your hair
Itis important to completely cover your entire head sothat all lice and eggs are exposed to the lotion, Be surethat each hair is coated from the scalp to the tip
Wait and Rinse
Allow product to stay on your hair and scalp for 10minutes after it has been applied, Use a timer or clockStart timing after you have completely covered yourhair and scalp with product.
After 10 minutes, rinse product completely from youhair and scalp using only water.
After rinsing, dry and style hair as usual. Wait 24 hoursbefore applying shampoo.

After treatment

Wash your hands after applying product.
-Nit combing is not necessary whentreating with product for it to work, but ifdesired, a fne-tooth comb or special nitcomb may be used to remove dead liceand nits.This is a single use product, Discard
bottle after use.Do not use again on the same personand same lice infestation without talkingto a healthcare provider frst.If infestation continues, see a doctor forother treatments.
Machine wash any bedding and clothingused by anyone having lice, Machinewash at high temperatures (150°F) andtumble in a hot dryer for 20 minutes.After fnishing treatment with licemedicine, check everyone in your famillyfor lice after one week. Considertreatment for those who have lice.

PACKAGE LABEL

Kills Lice:
Just once is all it takes

IVERMET
0.5% Lice Treatment Lotion

ONCE
10 MINUTES!
NO MESS

NET WT: 4 OZ (125 mL)